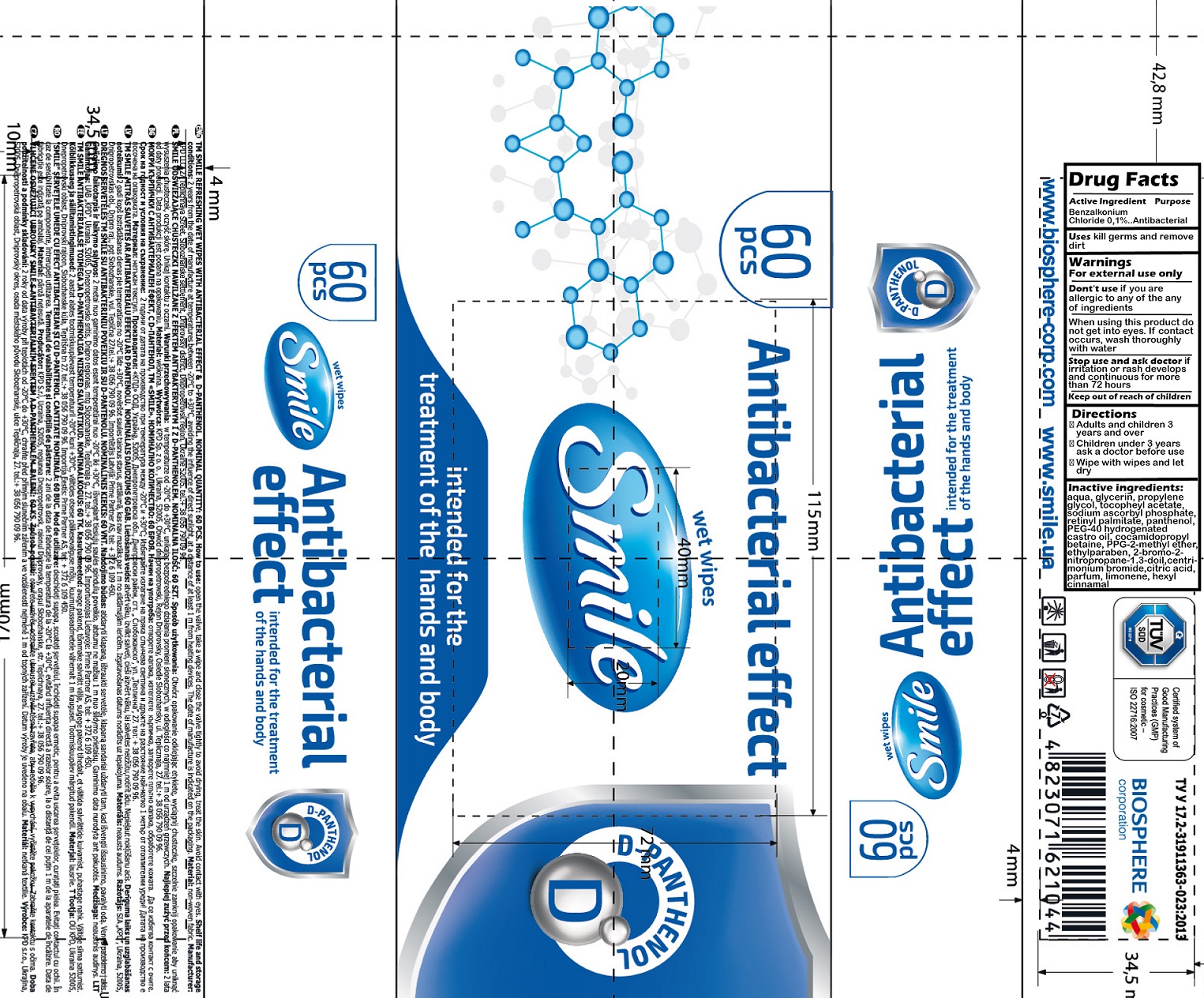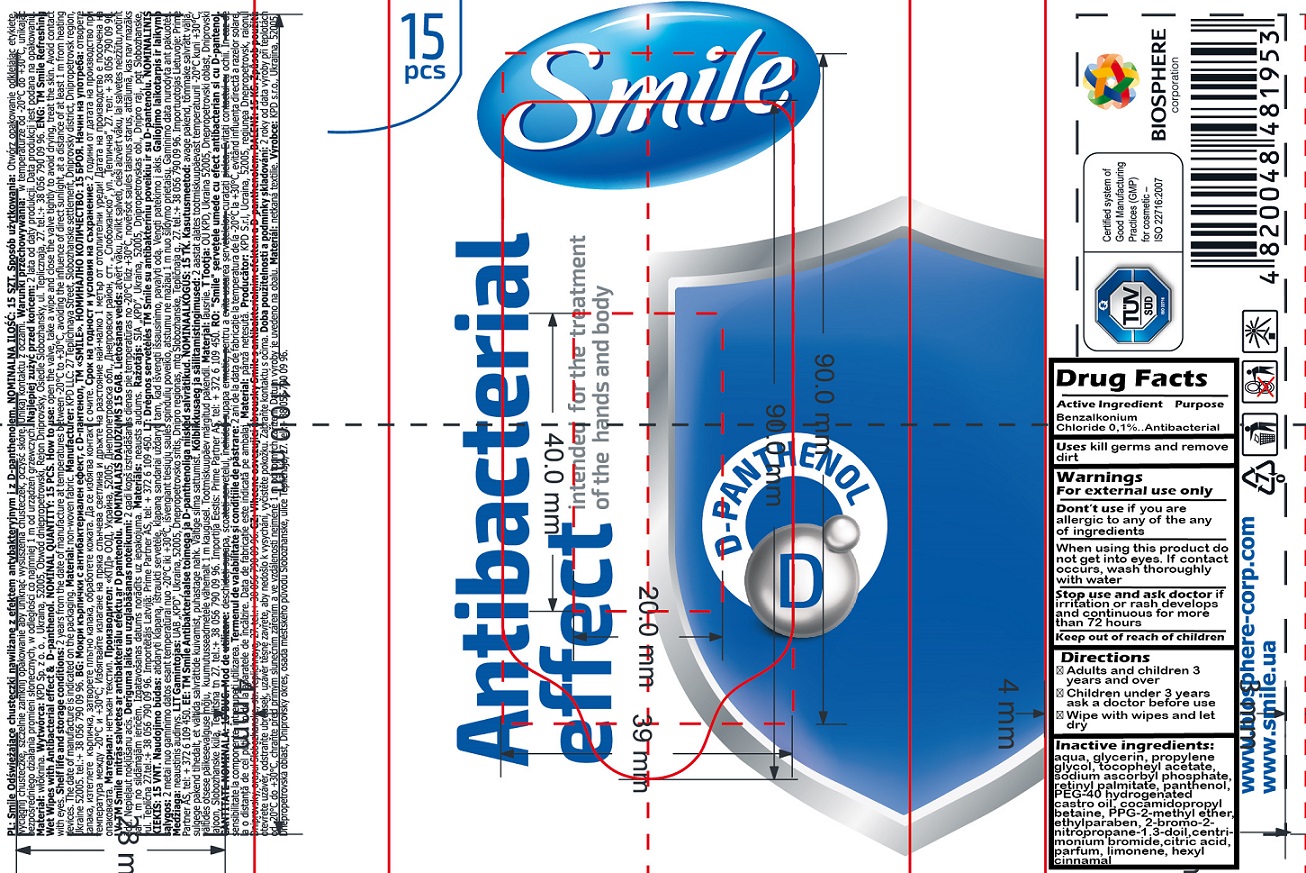 DRUG LABEL: Smile Antibacterial Wet Wipes D-panthenol
NDC: 81119-002 | Form: CLOTH
Manufacturer: KPD, Limited Liability Company
Category: otc | Type: HUMAN OTC DRUG LABEL
Date: 20201209

ACTIVE INGREDIENTS: BENZALKONIUM CHLORIDE 1 mg/1 mL
INACTIVE INGREDIENTS: WATER; GLYCERIN; PROPYLENE GLYCOL; .ALPHA.-TOCOPHEROL ACETATE; SODIUM ASCORBYL PHOSPHATE; VITAMIN A PALMITATE; PANTHENOL; COCAMIDOPROPYL BETAINE; ETHYLPARABEN; BRONOPOL; CETRIMONIUM BROMIDE; CITRIC ACID MONOHYDRATE; LIMONENE, (+)-; .ALPHA.-HEXYLCINNAMALDEHYDE; PPG-2 METHYL ETHER; POLYOXYL 40 HYDROGENATED CASTOR OIL

Smile Antibacterial Wet Wipes D-panthenol

Active Ingredient

Benzalkonium Chloride 0,1%

Purpose

Antibacterial

Uses

kill germs and remove dirt

Warnings

For external use only

Don't use

if you are alleric to any of the any of ingredients

When using this product

do not get into eyes. If contact occurs, wash thoroughly with water

Stop use and ask doctor

if irritation or rash develops and continuous for more than 72 hours

Directions

- Adults and children 3 years and over
- Children under 3 years ask a doctor before use
- Wipe with wipes and let dry

Inactive ingredients:

aqua, glycerin, propylene glycol, tocopheyl acetate, sodium ascorbyl phosphate, retinyl palmitate, panthenol, PEG-40 hydrogenated castro oil, cocamidopropyl betaine, PPG-2-methyl ether, ethylparaben, 2-bromo-2-nitropropane-1,3-doil, centrimonium bromide, citric acid, parfum, limonene, hexyl cinnamal